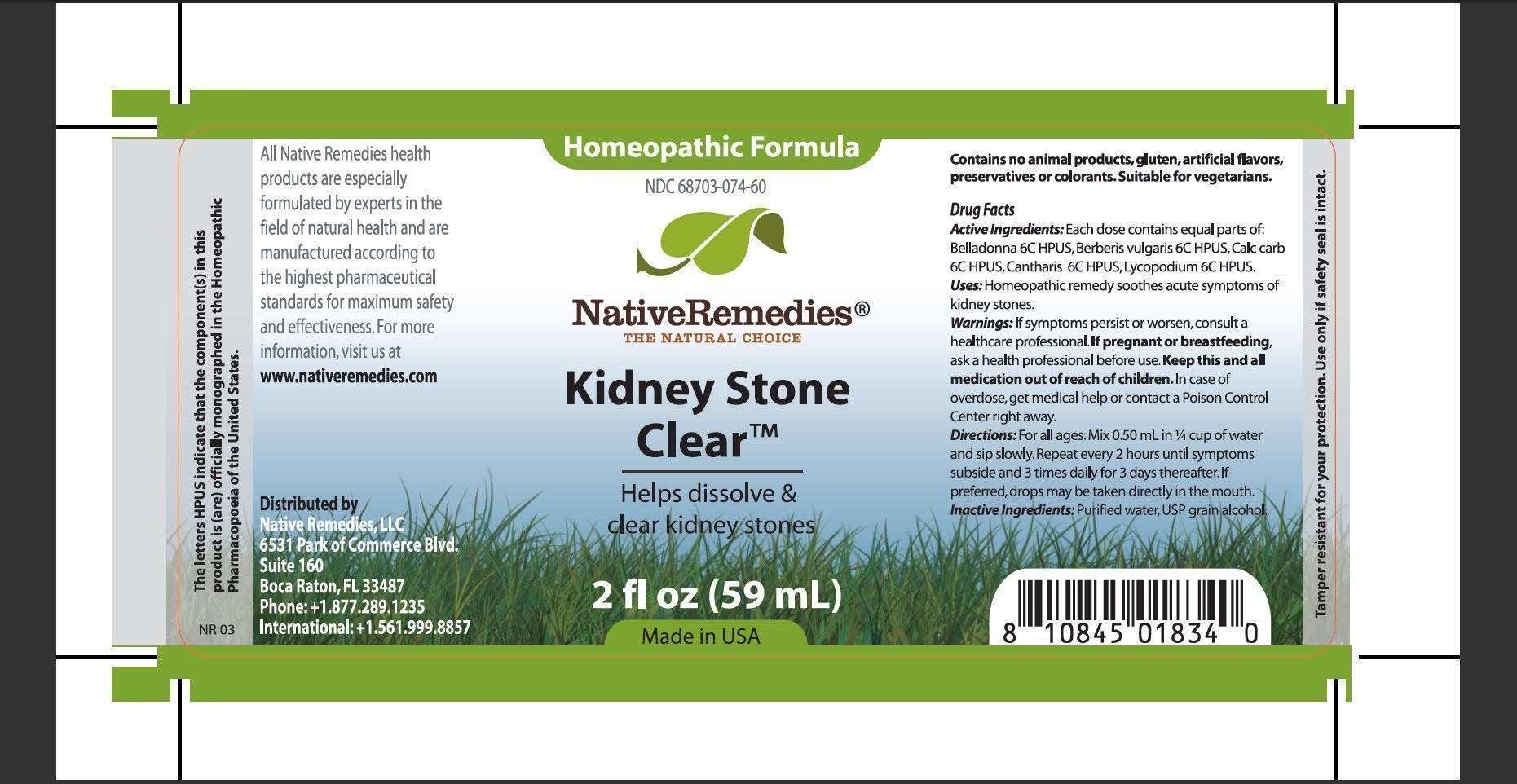 DRUG LABEL: Kidney Stone Clear
NDC: 68703-074 | Form: TINCTURE
Manufacturer: Native Remedies, LLC
Category: homeopathic | Type: HUMAN OTC DRUG LABEL
Date: 20130327

ACTIVE INGREDIENTS: ATROPA BELLADONNA 6 [hp_C]/1 mL; BERBERIS VULGARIS ROOT BARK 6 [hp_C]/1 mL; OYSTER SHELL CALCIUM CARBONATE, CRUDE 6 [hp_C]/1 mL; LYTTA VESICATORIA 6 [hp_C]/1 mL; LYCOPODIUM CLAVATUM SPORE 6 [hp_C]/1 mL
INACTIVE INGREDIENTS: WATER; ALCOHOL

Kidney Stone Clear

PURPOSE

Helps dissolve and clear kidney stones

ACTIVE INGREDIENT

Active Ingredients: Each dose contains equal parts of: Belladonna 6C HPUS, Berberis vulgaris 6C HPUS, Calc carb 6C HPUS, Cantharis 6C HPUS, Lycopodium 6C HPUS

INDICATIONS AND USAGE

Uses: Homeopathic remedy soothes acute symptoms of kidney stones

WARNINGS

Warnings: If symptoms persist or worsen, consult a healthcare professional

PREGNANCY OR BREAST FEEDING

If pregnant of breastfeeding, ask a health professional before use

KEEP OUT OF REACH OF CHILDREN

Keep this and all medications out of reach of children

OVERDOSAGE

In case of overdose, get medical help or contact a Poison Control Center right away

DOSAGE AND ADMINISTRATION

Directions: For all ages: Mix 0.50 mL in 1/4 cup of water and sip slowly. Repeat every 2 hours until symptoms subside and 3 times daily for 3 days thereafter. If preferred, drops may be taken directly in the mouth

Inactive Ingredients: Purified water, USP grain alcohol

PATIENT COUNSELING INFORMATION

The letters HPUS indicate that the component(s) in this product is (are) officially monographed in the Homeopathic Pharmacopoeia of the United States

All Native Remedies health products are especially formulated by experts int he field of natural health and are manufactured according to the highest pharmaceutical standards for maximum safety and effectiveness. For more information, visit us at www.nativeremedies.com

Distributed by
Native Remedies, LLC
6531 PArk of Commerce Blvd.
Suite 160
Boca Raton, FL 33487
Phone: +1.877.289.1235
International: +1.561.999.8857

Contains no animal products, gluten, artificial flavors, preservatives or colorants. Suitable for vegetarians

STORAGE AND HANDLING

Tamper resistant for your protection. Use only if safety seal is intact